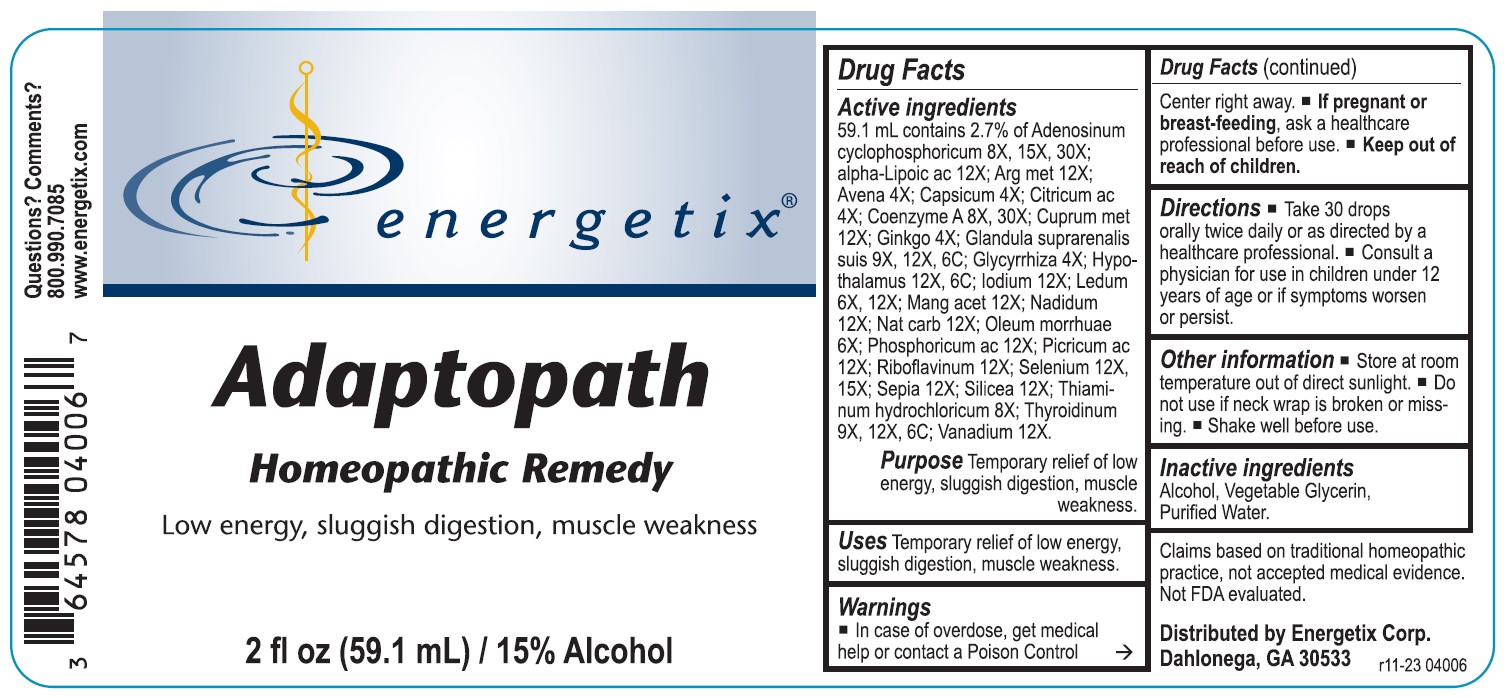 DRUG LABEL: Adaptopath
NDC: 64578-0095 | Form: LIQUID
Manufacturer: Energetix Corporation
Category: homeopathic | Type: HUMAN OTC DRUG LABEL
Date: 20241211

ACTIVE INGREDIENTS: ADENOSINE CYCLIC PHOSPHATE 8 [hp_X]/1 mL; .ALPHA.-LIPOIC ACID 12 [hp_X]/1 mL; SILVER 12 [hp_X]/1 mL; AVENA SATIVA FLOWERING TOP 4 [hp_X]/1 mL; CAPSICUM 4 [hp_X]/1 mL; ANHYDROUS CITRIC ACID 4 [hp_X]/1 mL; COENZYME A 8 [hp_X]/1 mL; COPPER 12 [hp_X]/1 mL; GINKGO 4 [hp_X]/1 mL; SUS SCROFA ADRENAL GLAND 9 [hp_X]/1 mL; GLYCYRRHIZA GLABRA 4 [hp_X]/1 mL; BOS TAURUS HYPOTHALAMUS 12 [hp_X]/1 mL; IODINE 12 [hp_X]/1 mL; LEDUM PALUSTRE TWIG 6 [hp_X]/1 mL; MANGANESE ACETATE TETRAHYDRATE 12 [hp_X]/1 mL; NADIDE 12 [hp_X]/1 mL; SODIUM CARBONATE 12 [hp_X]/1 mL; COD LIVER OIL 6 [hp_X]/1 mL; PHOSPHORIC ACID 12 [hp_X]/1 mL; PICRIC ACID 12 [hp_X]/1 mL; RIBOFLAVIN 12 [hp_X]/1 mL; SELENIUM 12 [hp_X]/1 mL; SEPIA OFFICINALIS JUICE 12 [hp_X]/1 mL; SILICON DIOXIDE 12 [hp_X]/1 mL; THIAMINE HYDROCHLORIDE 8 [hp_X]/1 mL; THYROID, BOVINE 9 [hp_X]/1 mL; VANADIUM 12 [hp_X]/1 mL
INACTIVE INGREDIENTS: WATER; GLYCERIN; ALCOHOL

Adaptopath

ACTIVE INGREDIENT

Active ingredients 59.1 mL contains 2.7% of Adenosinum cyclophosphoricum 8X, 15X, 30X; alpha-Lipoicum ac 12; Arg met 12X; Avena 4X; Capsicum 4X; Citricum ac 4X; Coenzyme A 8X, 30X; Cuprum met 12X; Ginkgo 4X; Glandula suprarenalis suis 9X, 12X, 6C; Glycyrrhiza 4X; Hypothalamus 12X, 6C; Iodium 12X; Ledum 6X, 12X; Mang acet 12X; Nadidum 12X; Nat carb 12X; Oleum morrhuae 6X; Phosphoricum ac 12X; Picricum ac 12X; Riboflavinum 12X; Selenium 12X, 15X; Sepia 12X; Silicea 12X; Thiaminum hydrochloricum 8X; Thyroidinum 9X, 12X, 6C; Vanadium 12X.

Claims based on traditional homeopathic practice, not accepted medical evidence. Not FDA evaluated.

Warnings

- In case of overdose, get medical help or contact a Poison Control Center right away.
- If pregnant or breast-feeding,ask a health professional before use.

Keep out of reach of children.

Directions

• Take 30 drops orally twice daily or as directed by a healthcare professional.

• Consult a physician for use in children under 12 years of age or if symptoms worsen or persist.

Other information

- Store at room temperature out of direct sunlight.
- Do not use if neck wrap is broken or missing.
- Shake well before use.

INDICATIONS AND USAGE

UsesTemporary relief of low energy, sluggish digestion, muscle weakness.

Inactive ingredientsAlcohol, Vegetable Glycerin, Purified Water

QUESTIONS

Distributed by Energetix Corp.

Dahlonega, GA 30533

Questions? 800.990.7085

www.energetix.com

PACKAGE LABEL

energetix

Adaptopath

Homeopathic Remedy

Low energy, sluggish digestion, muscle weakness

2 fl oz (59.1 mL) / 15% Alcohol

PURPOSE

Purpose Temporary relief of low energy, sluggish digestion, muscle weakness.